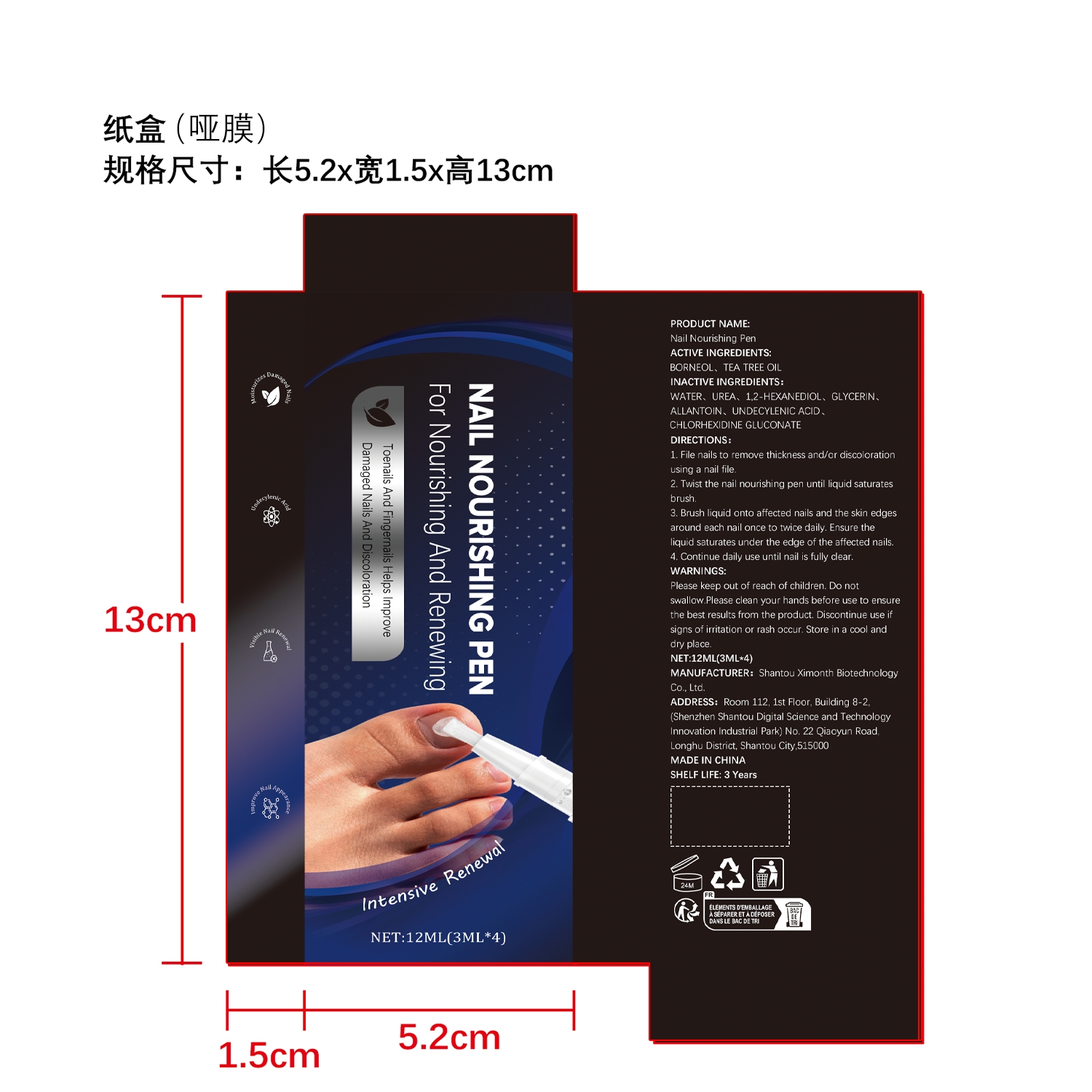 DRUG LABEL: Nail Nourishing Pen
NDC: 84989-018 | Form: LIQUID
Manufacturer: Shantou Ximonth Biotechnology Co., Ltd.
Category: otc | Type: HUMAN OTC DRUG LABEL
Date: 20260202

ACTIVE INGREDIENTS: BORNEOL 0.012 mg/12 mg; TEA TREE OIL 0.0024 mg/12 mg
INACTIVE INGREDIENTS: UNDECYLENIC ACID 0.0024 mg/12 mg; GLYCERIN 0.0024 mg/12 mg; ALLANTOIN 0.0024 mg/12 mg; WATER 11.3064 mg/12 mg; 1,2-HEXANEDIOL 0.06 mg/12 mg; CHLORHEXIDINE GLUCONATE 0.012 mg/12 mg; UREA 0.6 mg/12 mg

ACTIVE INGREDIENT

BORNEOL、TEA TREE OIL

PURPOSE

1. Nail Repair: Helps improve damaged fingernails and toenails.

2. Crack Reduction: Effectively reduces cracks and brittle nails.

3. Nail Strengthening: Improves nail strength and promotes long-term health.

4. Gloss Enhancement: Enhances nail luster and improves appearance.

5. Pen-shaped design allows for convenient and precise application anytime, anywhere.

6. Suitable for daily nail care, maintaining nail integrity.

7. Supports nail regeneration, promoting long-term healthy nail growth.

8. Gentle formula, gentle on nails and surrounding skin.

9. Absorbs quickly, leaving no sticky residue.

10. Suitable for both fingernails and toenails, providing comprehensive care.

11. Portable, perfect for on-the-go nail care.

12. Maintains nail integrity and reduces daily breakage.

13. Enhances the natural health of nails while also brightening them.

14. Easy to use, suitable for all ages.

15. With continued use, your nails will show visible health changes.

WHEN USING

Helps improve damaged fingernails and toenails; reduces nail cracking and brittleness; supports long-term nail regeneration and growth; improves nail health and luster; and improves nail appearance

WARNINGS

Please keep out of reach of children. Do not swallow.Please clean your hands before use to ensure the best results from the product. Discontinue use if signs of irritation or rash occur. Store in a cool and dry place.

DO NOT USE

Discontinue use if signs of irritation or rash occur.

STOP USE

Discontinue use if signs of irritation or rash occur.

KEEP OUT OF REACH OF CHILDREN

Please keep out of reach of children. Do not swallow

STORAGE AND HANDLING

Store in a cool and dry place.

INDICATIONS AND USAGE

Helps improve damaged fingernails and toenails; reduces nail cracking and brittleness; supports long-term nail regeneration and growth; improves nail health and luster; and improves nail appearance

INACTIVE INGREDIENT

WATER、UREA、1,2-HEXANEDIOL、GLYCERIN、ALLANTOIN、UNDECYLENIC ACID、CHLORHEXIDINE GLUCONATE

DOSAGE AND ADMINISTRATION

Helps improve damaged fingernails and toenails; reduces nail cracking and brittleness; supports long-term nail regeneration and growth; improves nail health and luster; and improves nail appearance